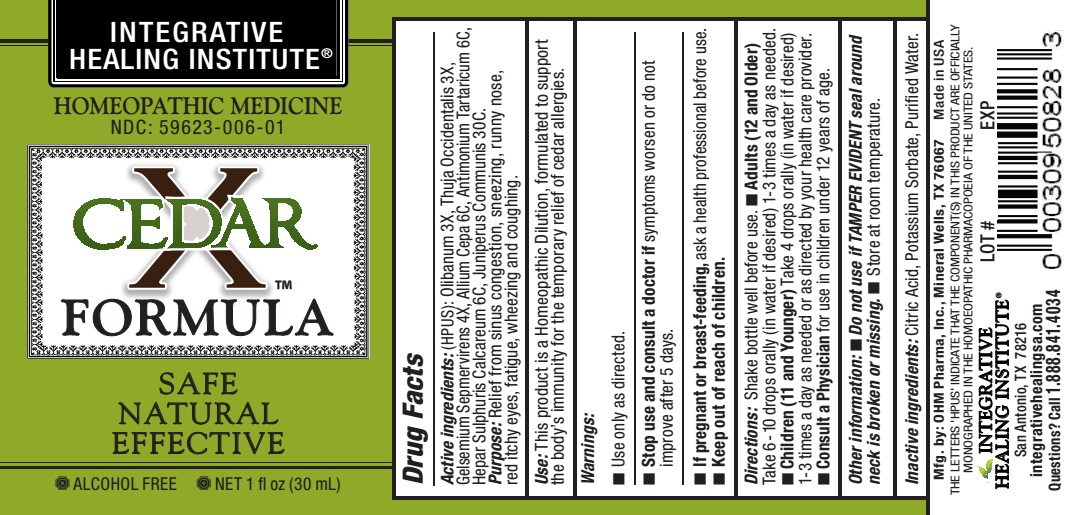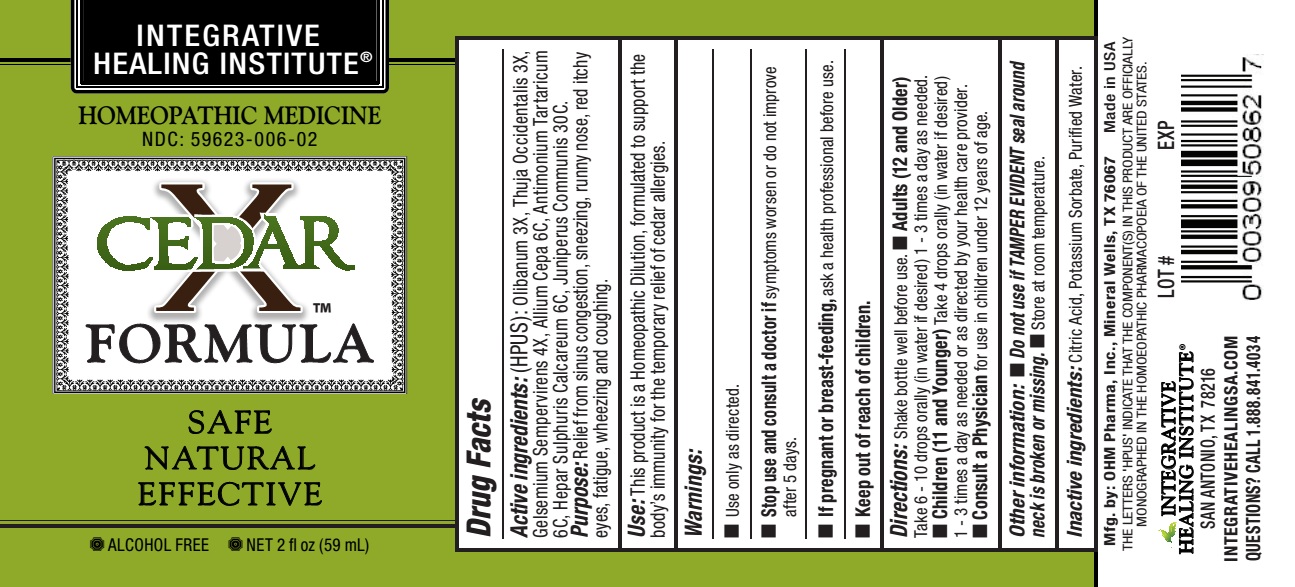 DRUG LABEL: Cedar X Formula

NDC: 59623-006 | Form: LIQUID
Manufacturer: Integrative Healing Institute, LLC
Category: homeopathic | Type: HUMAN OTC DRUG LABEL
Date: 20251017

ACTIVE INGREDIENTS: FRANKINCENSE 3 [hp_X]/1 mL; THUJA OCCIDENTALIS LEAFY TWIG 3 [hp_X]/1 mL; GELSEMIUM SEMPERVIRENS ROOT 4 [hp_X]/1 mL; ONION 6 [hp_C]/1 mL; ANTIMONY POTASSIUM TARTRATE 6 [hp_C]/1 mL; CALCIUM SULFIDE 6 [hp_C]/1 mL; JUNIPER BERRY 30 [hp_C]/1 mL
INACTIVE INGREDIENTS: WATER; CITRIC ACID MONOHYDRATE; POTASSIUM SORBATE

CEDAR X FORMULA

ACTIVE INGREDIENT

Active ingredients:Olibanum 3X, Thuja Occidentalis 3X, Gelsemium Sempervirens 4X, Allium Cepa 6C, Antimonium Tartaricum 6C, Hepar Sulphuris Calcareum 6C, Juniperus Communis 30C.

PURPOSE

Purpose:Relief from sinus congestion, sneezing, runny nose, red itchy eyes, fatigue, wheezing and coughing.

INDICATIONS AND USAGE

Use:This product is a Homeopathic Dilution, formulated to support the body's immunity for the temporary relief of cedar allergies.

Warnings:

- Use only as directed.
- Stop use and consult a doctor ifsymptoms worsen or do not improve after 5 days.
- If pregnant or breast-feeding,ask a health professional before use.

- Keep out of the reach of children.

DOSAGE AND ADMINISTRATION

Directions:Shake bottle well before use.

- Adults (12 and Older)Take 10 drops orally 1-3 times a day as needed.
- Children (11 and Younger)Take 6 drops orally 1-3 times a day as needed or as directed by your health care provider.
- Consult a Physicianfor use in children under 12 years of age.

Other information:

- Do not use if TAMPER EVIDENT seal around neck is broken or missing.
- Store at room temperature.

Inactive ingredients:Citric Acid, Potassium Sorbate, Purified Water.

OTHER SAFETY INFORMATION

Mfg. by:OHM Pharma, Inc., Mineral Wells, TX 76067

Made in USA

QUESTIONS

INTEGRATIVE HEALING INSTITUTE

San Antonio, TX 78216

integrativehealingsa.com

1.888.841.4034

PACKAGE LABEL

INTEGRATIVE HEALING INSTITUTE

HOMEOPATHIC MEDICINE

NDC: 59623-006-01

NDC: 59623-006-02

CEDAR X FORMULA

SAFE

NATURAL

EFFECTIVE

ALCOHOL FREE

NET 1 fl oz (30 mL)

NET 2 fl oz (60 mL)